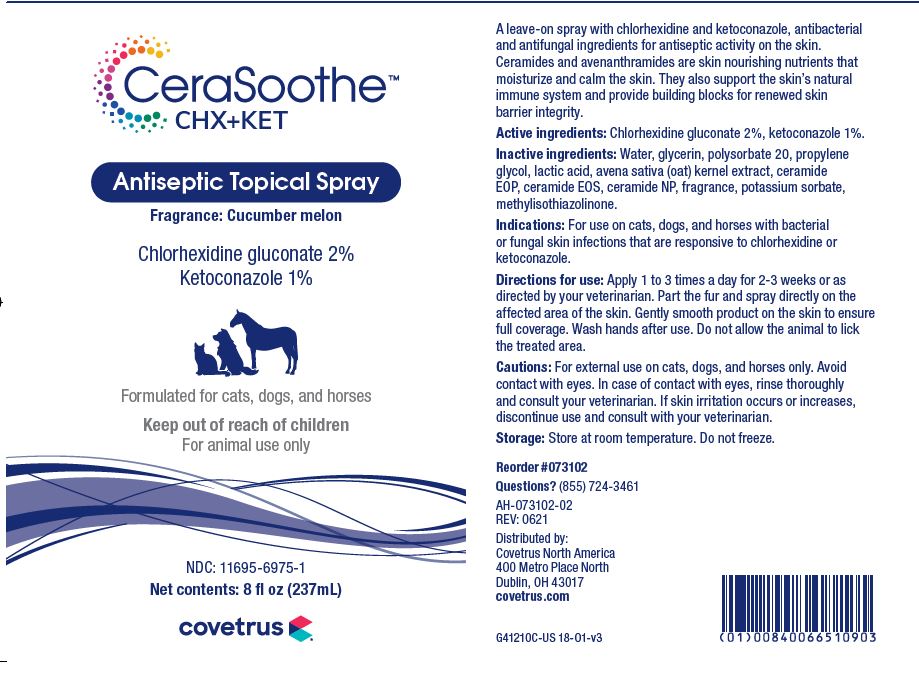 DRUG LABEL: CeraSoothe
NDC: 11695-6975 | Form: SPRAY
Manufacturer: Butler Animal Health Supply, LLC dba Covetrus North America
Category: animal | Type: OTC ANIMAL DRUG LABEL
Date: 20220502

ACTIVE INGREDIENTS: CHLORHEXIDINE GLUCONATE 20 mg/1 mL; KETOCONAZOLE 10 mg/1 mL
INACTIVE INGREDIENTS: WATER; GLYCERIN; POLYSORBATE 20; PROPYLENE GLYCOL; LACTIC ACID; AVENANTHRAMIDES; CERAMIDE 1; CERAMIDE EOS; CERAMIDE NP; POTASSIUM SORBATE; METHYLISOTHIAZOLINONE

DESCRIPTION

CeraSoothe CHX+KET

Antiseptic Topical Spray

Fragrance: Cucumber melon

A leave-on spray with chlorhexidine and ketoconazole, antibacterial and antifungal ingredients for antiseptic activity on the skin. Ceramides and avenanthramides are skin nourishing nutrients that moisturize and calm the skin. They also support the skin's natural immune system, and provide building blocks for renewed skin barrier integrity.

Active ingredients: Chlorhexidine gluconate 2%, ketoconazole 1%.

Inactive ingredients: Water, glycerin, polysorbate 20, propylene glycol, lactic acid, avena sativa (oat) kernal extract, ceramide EOP, ceramide EOS, ceramide NP, fragrance, potassium sorbate, methylisothiazolinone.

INDICATIONS AND USAGE

Indications: For use on cats, dogs and horses with bacterial or fungal skin infections that are responsive to chlorhexidine or ketoconazole.

Directions for use: Apply 1 to 3 times per day for 2-3 weeks or as directed by your veterinarian. Part the fur and spray directly on the affected area of the skin. Gently smooth product on the skin to ensure full coverage. Wash hands after use. Do not allow the animal to lick the treated area.

WARNINGS AND PRECAUTIONS

Cautions: For external use on cats, dogs and horses only. Avoid contact with eyes. In case of contact with eyes, rinse thoroughly and consult your veterinarian. If skin irritation occurs or increases, discontinue use and consult with your veterinarian.

Storage: Store at room temperature. Do not freeze.

QUESTIONS? (855) 724-3461

Distributed by:

Covetrus North America

400 Metro Place North

Dublin, OH 43017

covetrus.com

PRINCIPAL DISPLAY PANEL - 8 OUNCE (237 mL) Bottle

Inspired by veterinarians

CeraSoothe CHX+KET

Antiseptic Topical Spray

Fragrance: Cucumber melon

Chlorhexidine gluconate 2%

Ketoconazole 1%

Formulated for cats, dogs, and horses

Keep out of reach of children

For animal use only

NDC: 11695-6975-1

Net Contents: 8 fl oz (237 mL)

covetrus